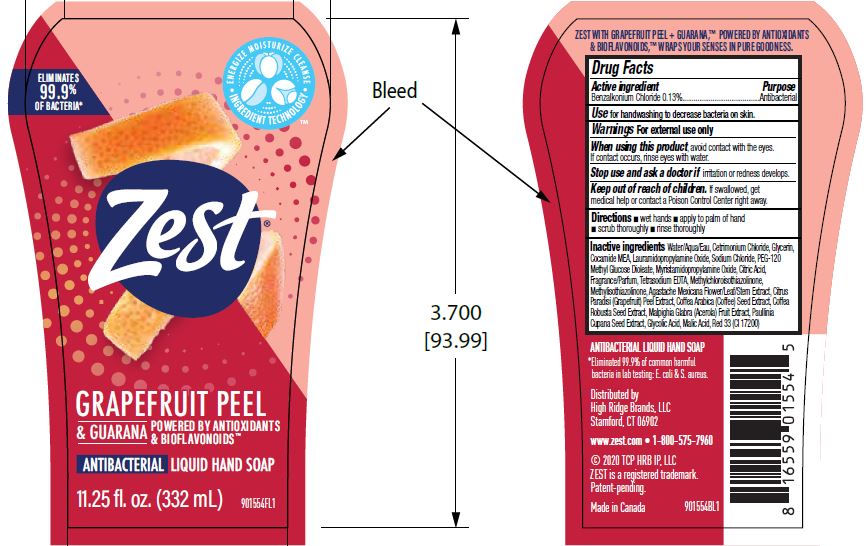 DRUG LABEL: Zest Antibacterial Liquid Hand
NDC: 81277-101 | Form: SOAP
Manufacturer: TCP HRB HOLDINGS LLC
Category: otc | Type: HUMAN OTC DRUG LABEL
Date: 20201216

ACTIVE INGREDIENTS: Benzalkonium Chloride 0.13 g/100 mL
INACTIVE INGREDIENTS: Water; Cetrimonium Chloride; Glycerin; COCO MONOETHANOLAMIDE; Lauramidopropylamine Oxide; Sodium Chloride; PEG-120 METHYL GLUCOSE DIOLEATE; MYRISTAMIDOPROPYLAMINE OXIDE; CITRIC ACID MONOHYDRATE; EDETATE SODIUM; METHYLCHLOROISOTHIAZOLINONE; METHYLISOTHIAZOLINONE; AGASTACHE FOENICULUM WHOLE; GRAPEFRUIT PEEL; ARABICA COFFEE BEAN; ROBUSTA COFFEE BEAN; ACEROLA; PAULLINIA CUPANA SEED; GLYCOLIC ACID; MALIC ACID; D&C RED NO. 33

Zest Antibacterial Liquid Hand Soap - Grapefruit Peel

Active ingredient

Benzalkonium Chloride 0.13%

Purpose

Antibacterial

USE

For handwashing to decrease bacteria on the skin.

Warnings

FOR EXTERNAL USE ONLY.

WHEN USING THIS PRODUCT, AVOID CONTACT WITH THE EYES. IF CONTACT OCCURS, RINSE EYES WITH WATER.

STOP USE AND ASK A DOCTOR IF IRRITATION OR REDNESS DEVELOPS.

Keep out of reach of children If swallowed, get medical help or contact a Poison Control Center right away.

Directions

- wet hands
- apply to palm of hand
- scrub thoroughly
- rinse thoroughly

Inactive ingredients

Water/Aqua/Eau, Cetrimonium Chloride, Glycerin, Cocamide MEA, Lauramidopropylamine Oxide, Sodium Chloride, PEG-120 Methyl Glucose Dioleate, Myristamidopropylamine Oxide, Citric Acid, Fragrance/Parfum, Tetrasodium EDTA, Methylchloroisothiazolinone, Methylisothiazolinone, Agastache Mexicana Flower/Leaf/Stem Extract, Citrus Paradisi (Grapefruit) Peel Extract, Coffea Arabica (Coffee) Seed Extract, Coffea Robusta Seed Extract, Malpighia Glabra (Acerola) Fruit Extract, Paullinia Cupana Seed Extract, Glycolic Acid, Malic Acid, Red 33 (CI 17200)